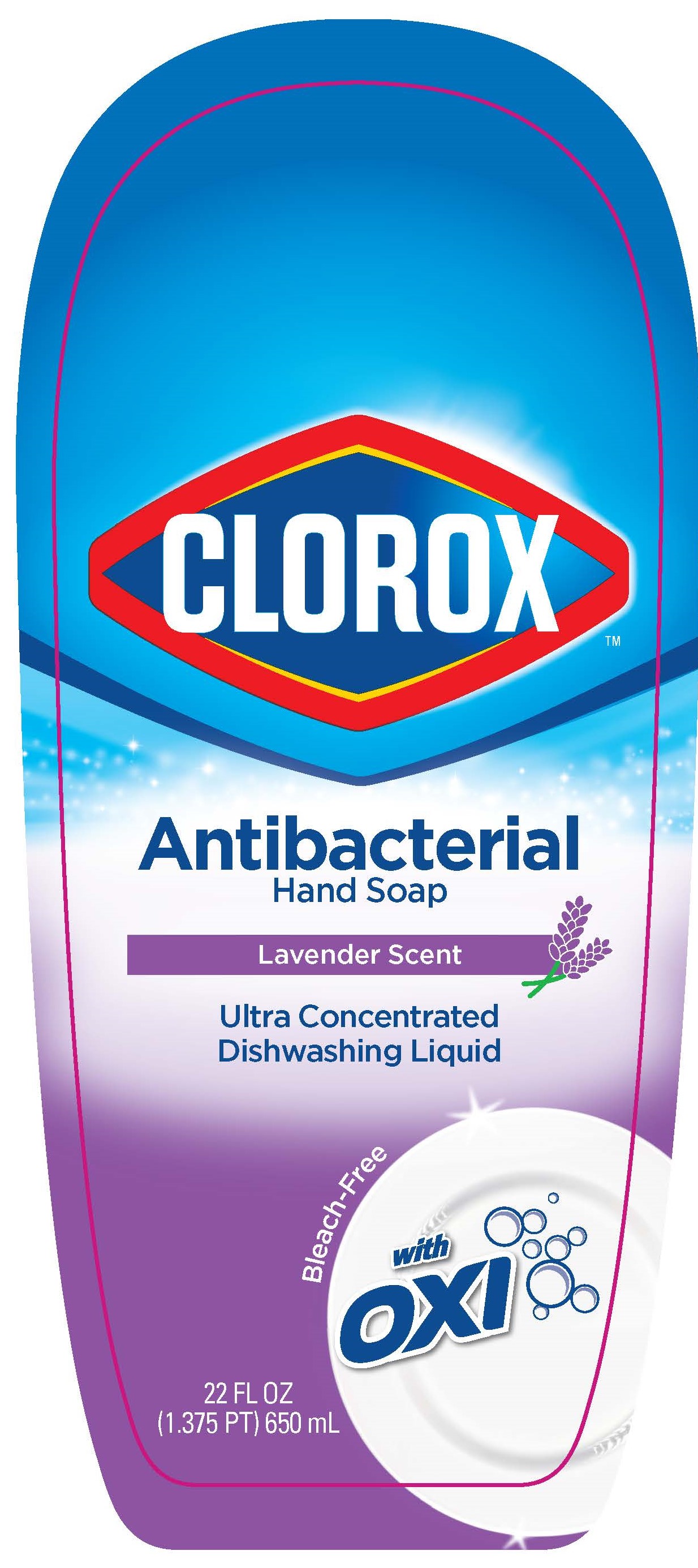 DRUG LABEL: Clorox Antimicrobial
NDC: 69540-0031 | Form: SOAP
Manufacturer: Brand Buzz LLC
Category: otc | Type: HUMAN OTC DRUG LABEL
Date: 20230202

ACTIVE INGREDIENTS: BENZALKONIUM CHLORIDE 0.13 g/100 mL
INACTIVE INGREDIENTS: SODIUM LAURETH SULFATE; SODIUM CHLORIDE; SODIUM C14-16 OLEFIN SULFONATE; COCAMIDOPROPYL BETAINE; C12-14 PARETH-12; EDETATE DISODIUM ANHYDROUS; SODIUM BICARBONATE; METHYLCHLOROISOTHIAZOLINONE; WATER; FD&C BLUE NO. 1; D&C RED NO. 33

Clorox Antibacterial Hand Soap (Orange Fusion)

Active ingredient

Benzalkonium Chloride 0.13%

Purpose

Antibacterial

Use

- For handwashing to decrease bacteria on skin

Warnings

For external use only.

In case of accidental ingestion, drink a glass of water to dilute. If eye contact occurs, rinse thoroughly with water. If irritation persists, contact a Poison Control Center right away.

Keep out of reach of children.

Directions

- Apply onto wet hands, lather for 30 seconds and rinse thoroughly.

Other Information

- Avoid freezing and excessive heat above 40℃ (104℉).

Inactive ingredients

Water, Sodium Laureth Sulfate, Sodium Chlroride, Sodium C14-16 Olefin Sulfonate, Cocamidopropyl Betaine, Laureth-3, Sodium Bicarbonate, Disodium EDTA, Fragrance, Methylchloroisothiazolinone, Methylisothiazoline, Blue 1 (Ci 42090), Red 33 (Ci 17200).

Do not add bleach.

Not for use in dishwashers.

PHOSPATE-FREE

BLEACH-FREE

Distributed by: Brand Buzz LLC., 1407 Broadway, New York, NY 10018

Clorox and logo are registered trademarks of the Clorox Company and are used under license by Brand Buzz LLC.
All Rights Reserved.

Questions or Comments?

Visit us at www.brandbuzzcp.com or call us at: 1-888-508-4750

For more product ingredient information, visit www.brandbuzzcp.com/ingredients

PACKAGE LABEL

Clorox

Antimicrobial

HandSoap

Ultra Concentrated Dishwashing Liquid

Lavender Scent

with Oxi

Bleach-Free

8FL OZ

(0.5 PT) 236 mL

Label